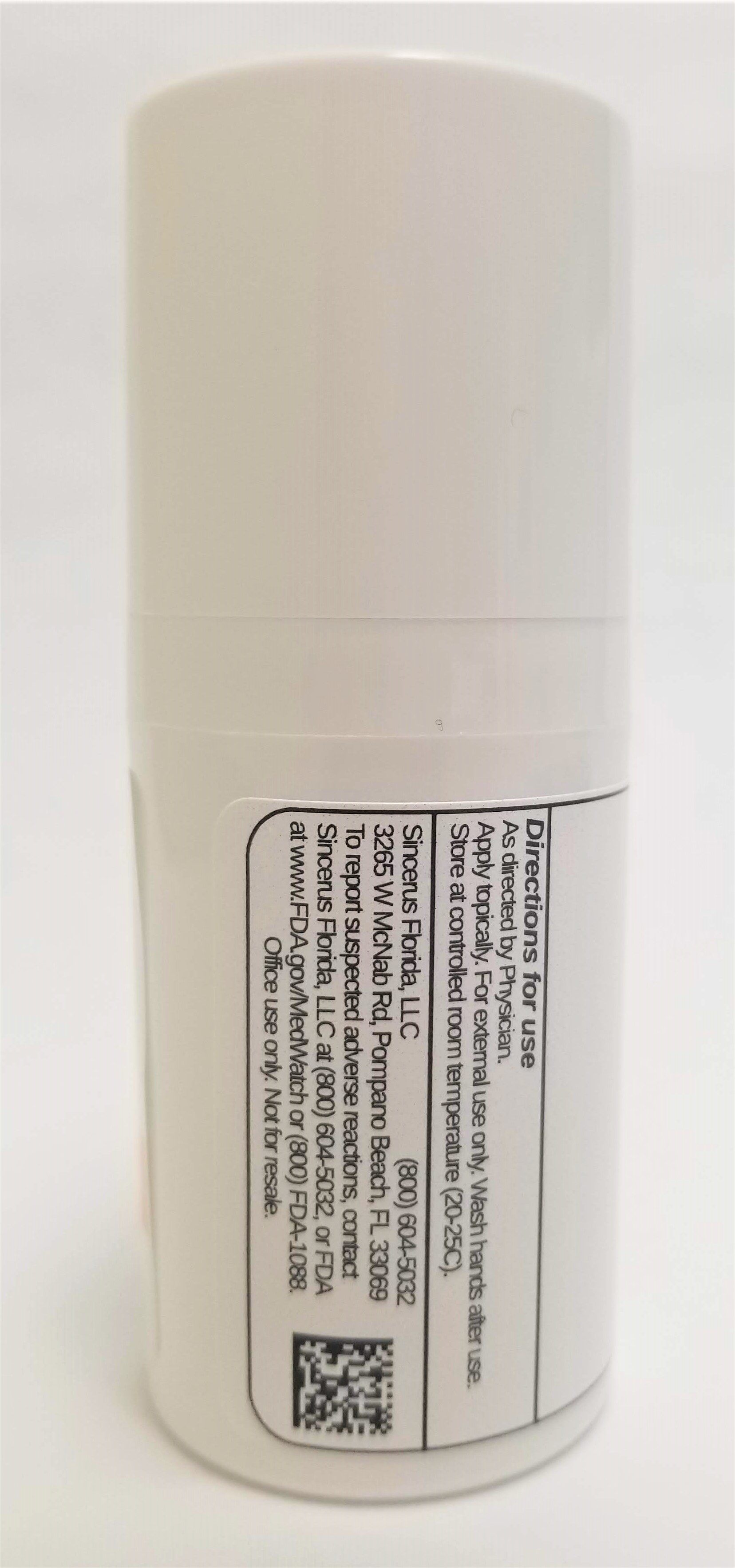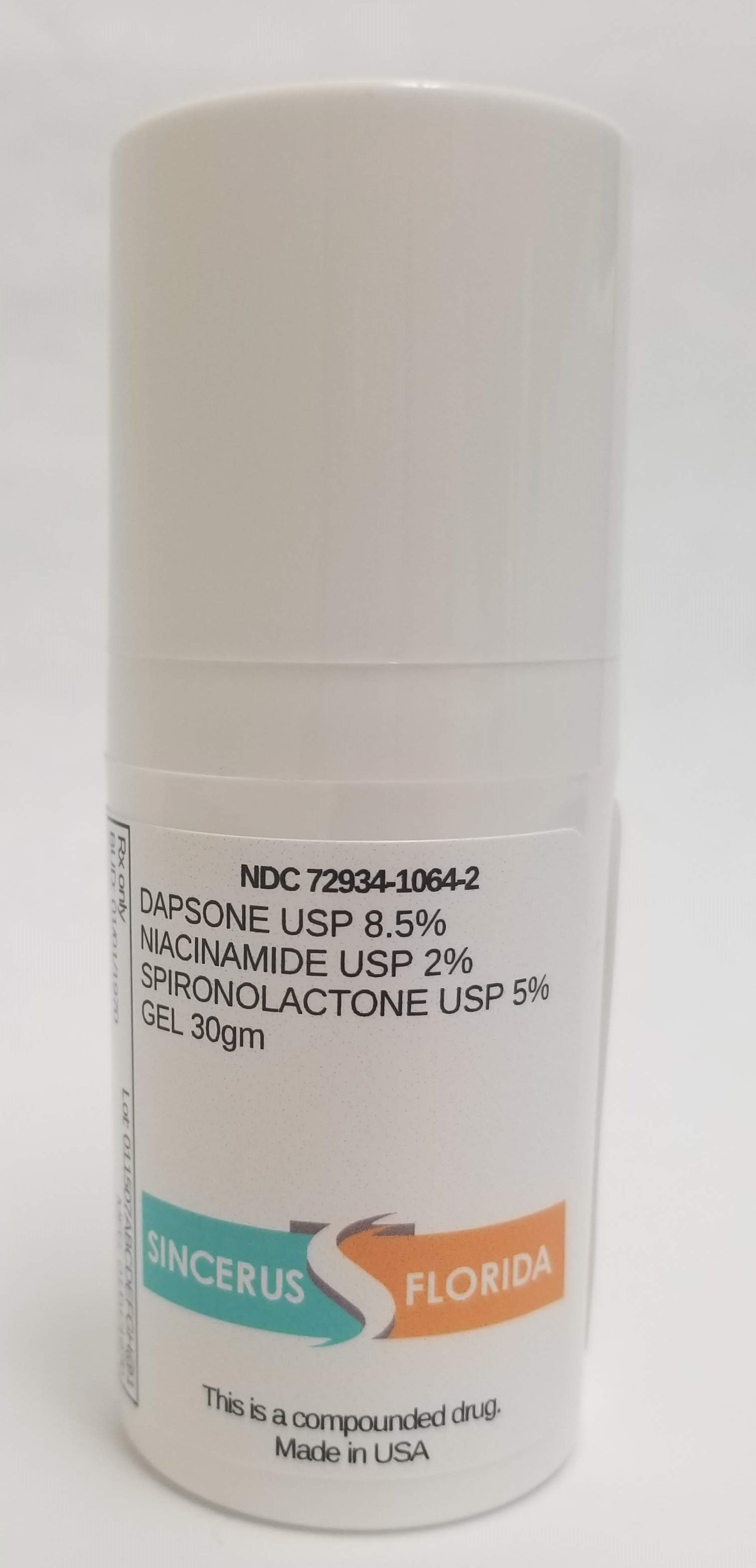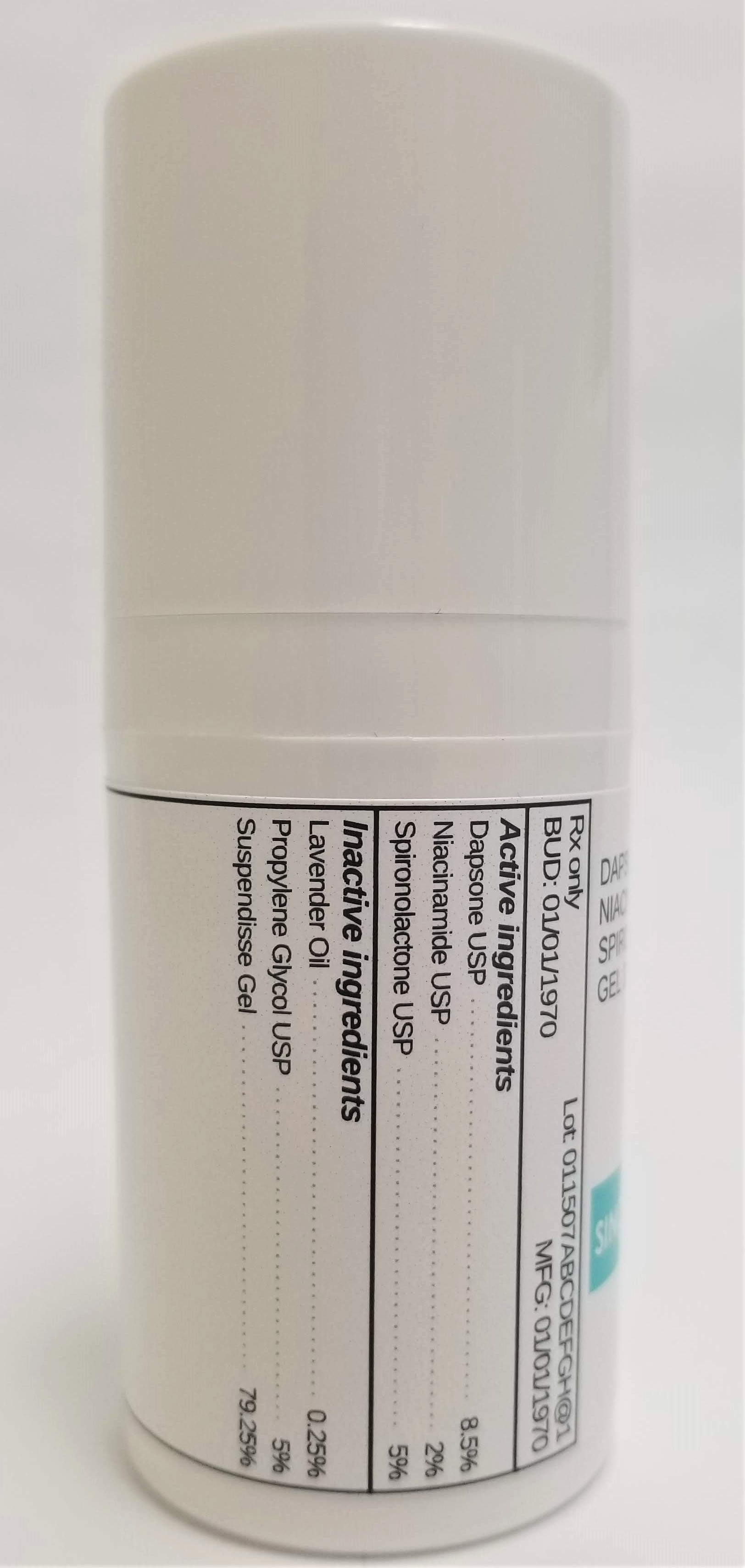 DRUG LABEL: DAPSONE 8.5% / NIACINAMIDE 2% / SPIRONOLACTONE 5%
NDC: 72934-1064 | Form: GEL
Manufacturer: Sincerus Florida, LLC
Category: prescription | Type: HUMAN PRESCRIPTION DRUG LABEL
Date: 20190509

ACTIVE INGREDIENTS: SPIRONOLACTONE 5 g/100 g; DAPSONE 8.5 g/100 g; NIACINAMIDE 2 g/100 g

DAPSONE 8.5% / NIACINAMIDE 2% / SPIRONOLACTONE 5%